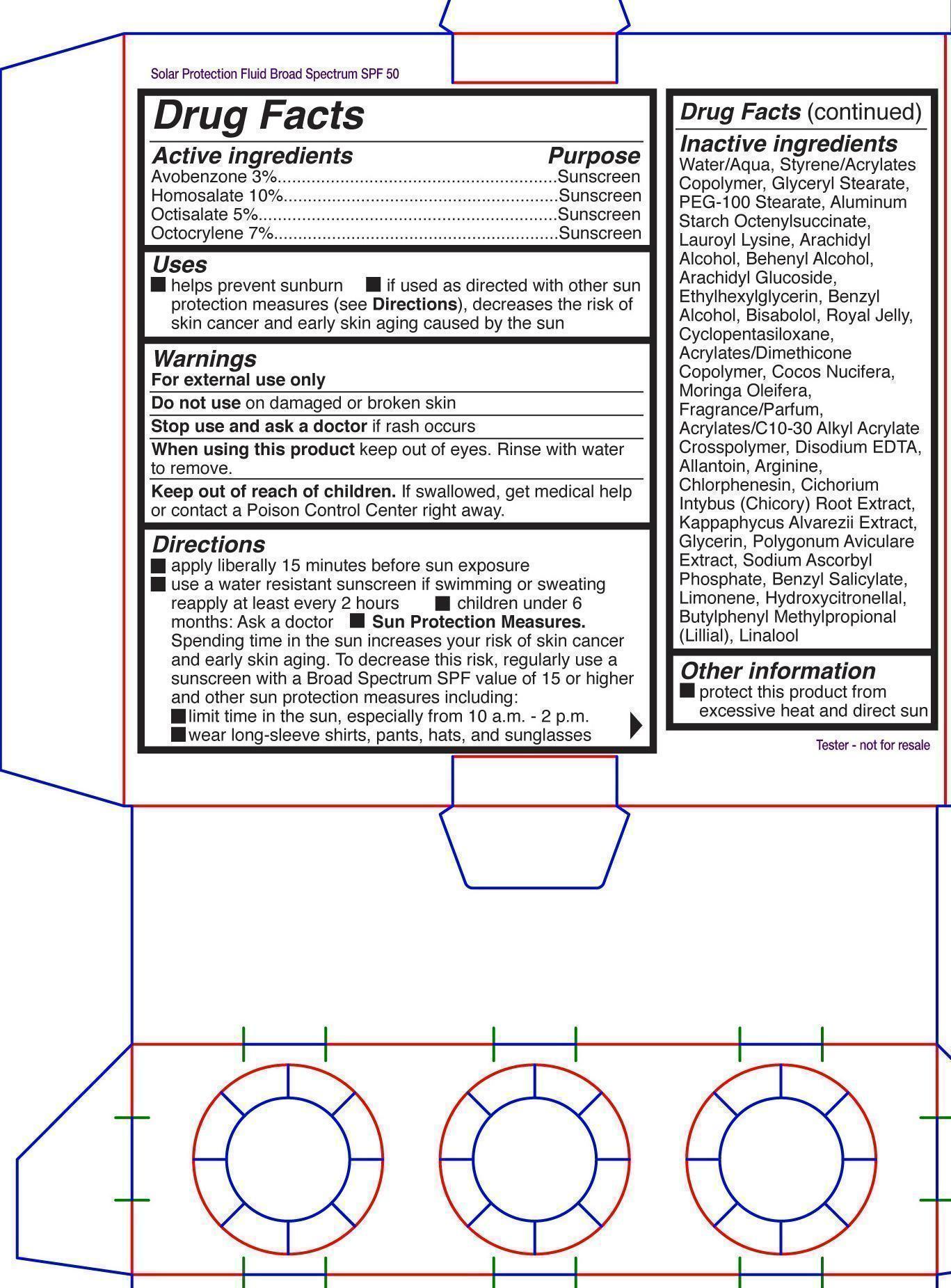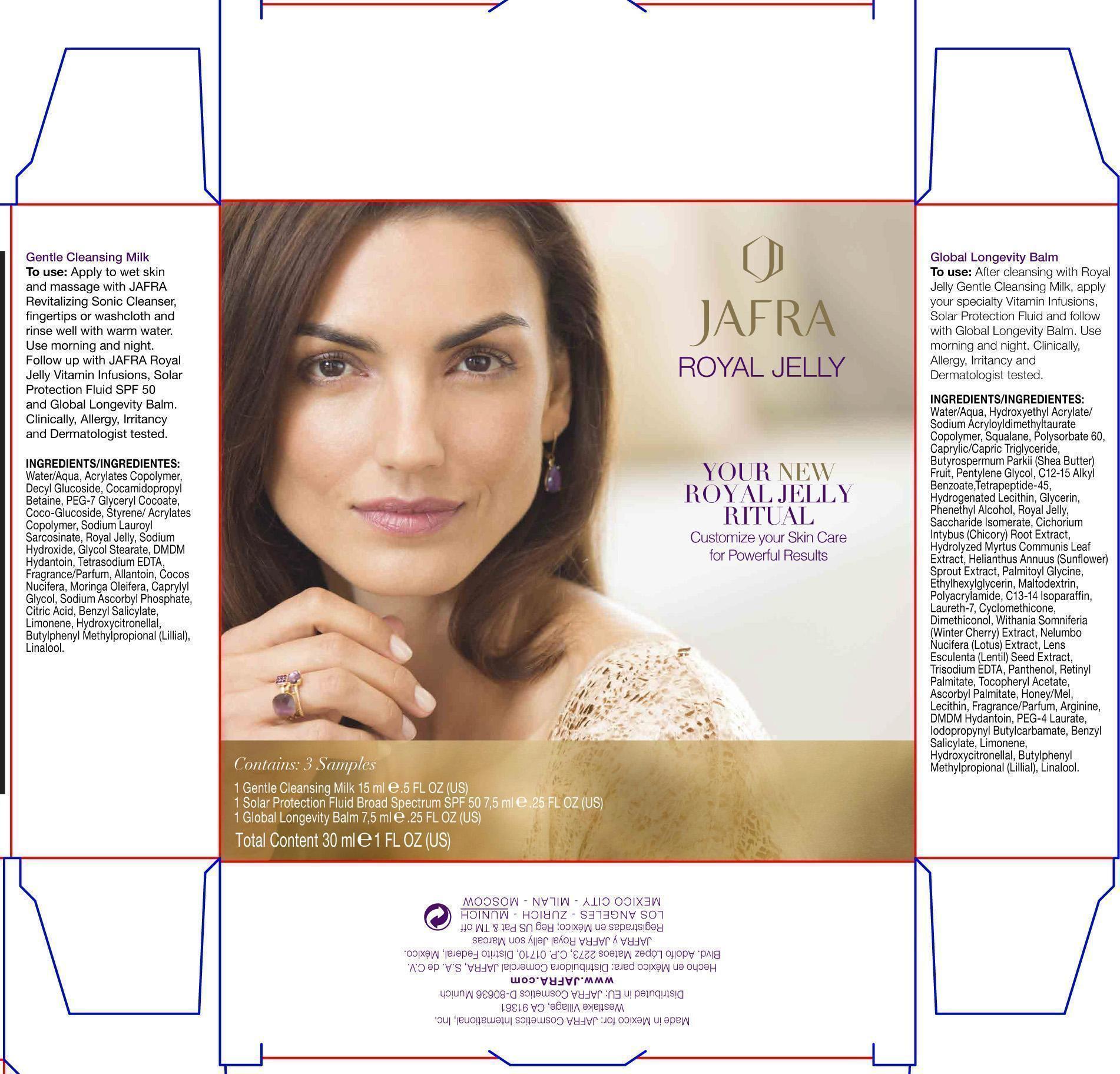 DRUG LABEL: Royal Jelly Kit

NDC: 68828-242 | Form: KIT | Route: TOPICAL
Manufacturer: JAFRA COSMETICS INTERNATIONAL
Category: otc | Type: HUMAN OTC DRUG LABEL
Date: 20200622

ACTIVE INGREDIENTS: AVOBENZONE 3 g/100 mL; HOMOSALATE 10 g/100 mL; OCTISALATE 5 g/100 mL; OCTOCRYLENE 7 g/100 mL
INACTIVE INGREDIENTS: WATER; GLYCERYL MONOSTEARATE; PEG-100 STEARATE; ALUMINUM STARCH OCTENYLSUCCINATE; LAUROYL LYSINE; ARACHIDYL ALCOHOL; DOCOSANOL; ARACHIDYL GLUCOSIDE; ETHYLHEXYLGLYCERIN; BENZYL ALCOHOL; LEVOMENOL; ROYAL JELLY; CYCLOMETHICONE 5; COCONUT; MORINGA OLEIFERA LEAF; EDETATE DISODIUM; ALLANTOIN; ARGININE; CHLORPHENESIN; CHICORY ROOT; KAPPAPHYCUS ALVAREZII; GLYCERIN; POLYGONUM AVICULARE TOP; SODIUM ASCORBYL PHOSPHATE; BENZYL SALICYLATE; LIMONENE, (+)-; HYDROXYCITRONELLOL; BUTYLPHENYL METHYLPROPIONAL; LINALOOL, (+)-

Jafra Royal Jelly Kit

Active ingredients Purpose

Avobenzone 3% Sunscreen

Homosalatate 10% Sunscreen

Octisalate 5% Sunscreen

Octocrylene 7% Sunscreen

Uses

helps prevent sunburn

If used as directed with other sun protection measures (see Directions), decreases the risk of skin cancer and early skin aging caused by the sun

KEEP OUT OF REACH OF CHILDREN

Keep out of children. If swallowed, get medical help or contact a Poison Control Center right away.

Stop use and ask a doctor if rash occurs

Warnings

For external Use only

Do not use on damaged or broken skin

When using this product keep out of eyes. Rinse with water to remove.

Directions

apply liberally 15 minutes before sun exposure

Use a water resistant sunscreen if swimming or sweating

reapply at least every 2 hours

Children under 6 months: ask a doctor

Sun Protection Measures. Spending time in the sun increases your risk of skin cancer and early skin aging. To decrease this risk, regularly use a sunscreen with a Broad Spectrum SPF value of 15 or higher and other sun protection measures including:

limit time in the sun, especially 10a.m. - 2 p.m.

wear long-sleeve shirts, pants, hats and sunglasses

Inactive ingredients

Water/Aqua, Styrene/Acrylates Copolymer, Glyceryl Stearate, PEG-100 Stearate, Aluminum Starch Octenylsuccinate, Lauroyl Lysine, Arachidyl Alcohol, Behenyl Alcohol, Arachidyl Glucoside,Ethylhexylglycerin, Benzyl Alcohol, Bisabolol, Royal Jelly, Cyclopentasiloxane, Acrylates/Dimethicone Copolymer, Cocos Nucifera, Moringa Oleifera, Fragrance/Parfum, Acrylates/C10-30 Alkyl Acrylate Crosspolymer, Disodium EDTA, Allantoin, Arginine, Chlorphenesin, Cichorium Intybus (Chicory) Root Extract, Kappaphycus Alvarezii Extract, Glycerin, Polygonum Aviculare Extract, Sodium Ascorbyl Phosphate, Benzyl Salicylate, Limonene, Hydroxycitronellal, Butylphenyl Methylpropional (Lillial), Linalool

PACKAGE LABEL

Jafra Royal Jelly

Total Content 30 ml 1 FL OZ